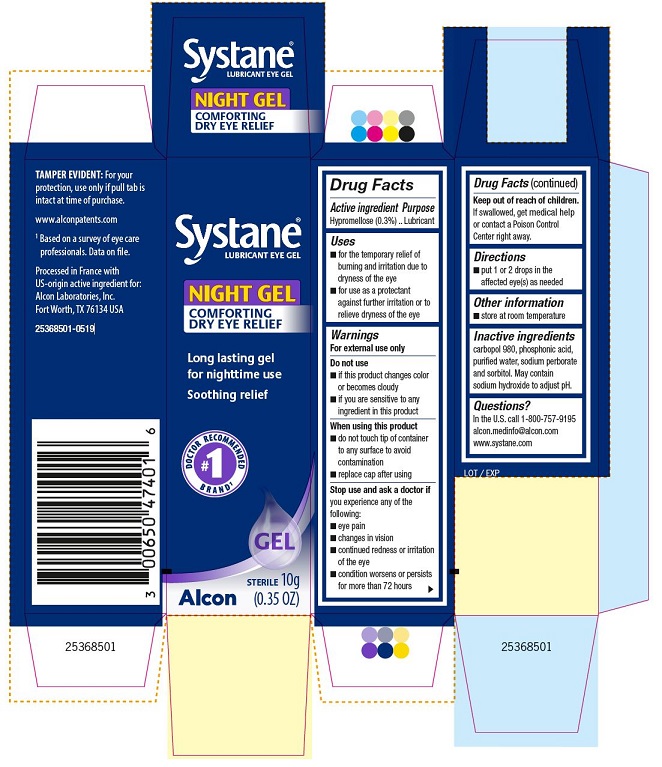 DRUG LABEL: Systane
NDC: 0065-0474 | Form: GEL
Manufacturer: Alcon Laboratories, Inc.
Category: otc | Type: HUMAN OTC DRUG LABEL
Date: 20231215

ACTIVE INGREDIENTS: Hypromellose 2910 (4000 Mpa.s) 3 mg/1 g
INACTIVE INGREDIENTS: Carbomer Homopolymer Type C (allyl Pentaerythritol Crosslinked); Phosphonic Acid; Water; Sodium Perborate; Sorbitol; Sodium Hydroxide

Drug Facts

ACTIVE INGREDIENT

Active ingredient | Purpose
Hypromellose (0.3%) | Lubricant

Uses

- for the temporary relief of burning and irritation due to dryness of the eye
- for use as a protectant against further irritation or to relieve dryness of the eye

Warnings

For external use only

Do not use

- if this product changes color or becomes cloudy
- if you are sensitive to any ingredient in this product

When using this product

- do not touch tip of container to any surface to avoid contamination
- replace cap after using

Stop use and ask a doctor if you experience any of the following:

- eye pain
- changes in vision
- continued redness or irritation of the eye
- condition worsens or persists for more than 72 hours

Keep out of reach of children.

If swallowed, get medical help or contact a Poison Control Center right away.

Directions

- put 1 or 2 drops in the affected eye(s) as needed

Other information

- store at room temperature

Inactive ingredients

carbopol 980, phosphonic acid, purified water, sodium perborate and sorbitol. May contain sodium hydroxide to adjust pH.

Questions?

In the U.S. call 1-800-757-9195
alcon.medinfo@alcon.com
www.systane.com

PRINCIPAL DISPLAY PANEL

Systane®
LUBRICANT EYE GEL
NIGHT GEL
COMFORTING
DRY EYE RELIEF
Long lasting gel
for nighttime use
Soothing relief
#1 DOCTOR RECOMMENDED BRAND^1
GEL
Alcon
STERILE 10g
(0.35 OZ)
TAMPER EVIDENT: For your
protection, use only if pull tab is
intact at time of purchase.
www.alconpatents.com
^1 Based on a survey of eye care
professionals. Data on file.
Processed in France with
US-origin active ingredient for:
Alcon Laboratories, Inc.
Fort Worth, TX 76134 USA
25368501-0519
25368501

LOT / EXP